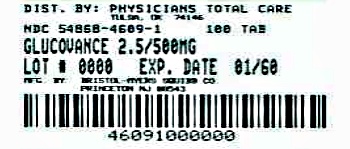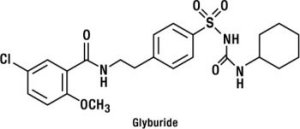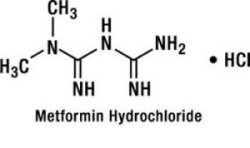 DRUG LABEL: GLUCOVANCE
NDC: 54868-4609 | Form: TABLET, FILM COATED
Manufacturer: Physicians Total Care, Inc.
Category: prescription | Type: HUMAN PRESCRIPTION DRUG LABEL
Date: 20120423

ACTIVE INGREDIENTS: glyburide 2.5 mg/1 1; metformin hydrochloride 500 mg/1 1
INACTIVE INGREDIENTS: cellulose, microcrystalline; povidone; croscarmellose sodium; magnesium stearate

GLUCOVANCE®
(Glyburide and Metformin HCl) Tablets

1.25 mg/250 mg
2.5 mg/500 mg
5 mg/500 mg

DESCRIPTION

GLUCOVANCE® (Glyburide and Metformin HCl) Tablets contain 2 oral antihyperglycemic drugs used in the management of type 2 diabetes, glyburide and metformin hydrochloride.

Glyburide is an oral antihyperglycemic drug of the sulfonylurea class. The chemical name for glyburide is 1-[[p-[2-(5-chloro-o-anisamido)ethyl]phenyl]sulfonyl]-3-cyclo-hexylurea. Glyburide is a white to off-white crystalline compound with a molecular formula of C23H28ClN3O5S and a molecular weight of 494.01. The glyburide used in GLUCOVANCE has a particle size distribution of 25% undersize value not more than 6 µm, 50% undersize value not more than 7 to 10 µm, and 75% undersize value not more than 21 µm. The structural formula is represented below.

Metformin hydrochloride is an oral antihyperglycemic drug used in the management of type 2 diabetes. Metformin hydrochloride (N,N-dimethylimidodicarbonimidic diamide monohydrochloride) is not chemically or pharmacologically related to sulfonylureas, thiazolidinediones, or α-glucosidase inhibitors. It is a white to off-white crystalline compound with a molecular formula of C4H12ClN5 (monohydrochloride) and a molecular weight of 165.63. Metformin hydrochloride is freely soluble in water and is practically insoluble in acetone, ether, and chloroform. The pKa of metformin is 12.4. The pH of a 1% aqueous solution of metformin hydrochloride is 6.68. The structural formula is as shown:

GLUCOVANCE is available for oral administration in tablets containing 1.25 mg glyburide with 250 mg metformin hydrochloride, 2.5 mg glyburide with 500 mg metformin hydrochloride, and 5 mg glyburide with 500 mg metformin hydrochloride. In addition, each tablet contains the following inactive ingredients: microcrystalline cellulose, povidone, croscarmellose sodium, and magnesium stearate. The tablets are film coated, which provides color differentiation.

CLINICAL PHARMACOLOGY

Mechanism of Action

GLUCOVANCE combines glyburide and metformin hydrochloride, 2 antihyperglycemic agents with complementary mechanisms of action, to improve glycemic control in patients with type 2 diabetes.

Glyburide appears to lower blood glucose acutely by stimulating the release of insulin from the pancreas, an effect dependent upon functioning beta cells in the pancreatic islets. The mechanism by which glyburide lowers blood glucose during long-term administration has not been clearly established. With chronic administration in patients with type 2 diabetes, the blood glucose-lowering effect persists despite a gradual decline in the insulin secretory response to the drug. Extrapancreatic effects may be involved in the mechanism of action of oral sulfonylurea hypoglycemic drugs.

Metformin hydrochloride is an antihyperglycemic agent that improves glucose tolerance in patients with type 2 diabetes, lowering both basal and postprandial plasma glucose. Metformin hydrochloride decreases hepatic glucose production, decreases intestinal absorption of glucose, and improves insulin sensitivity by increasing peripheral glucose uptake and utilization.

Pharmacokinetics

Absorption and Bioavailability

GLUCOVANCE

In bioavailability studies of GLUCOVANCE 2.5 mg/500 mg and 5 mg/500 mg, the mean area under the plasma concentration versus time curve (AUC) for the glyburide component was 18% and 7%, respectively, greater than that of the Micronase® brand of glyburide coadministered with metformin. The glyburide component of GLUCOVANCE, therefore, is not bioequivalent to Micronase®. The metformin component of GLUCOVANCE is bioequivalent to metformin coadministered with glyburide.

Following administration of a single GLUCOVANCE 5 mg/500 mg tablet with either a 20% glucose solution or a 20% glucose solution with food, there was no effect of food on the Cmax and a relatively small effect of food on the AUC of the glyburide component. The Tmax for the glyburide component was shortened from 7.5 hours to 2.75 hours with food compared to the same tablet strength administered fasting with a 20% glucose solution. The clinical significance of an earlier Tmax for glyburide after food is not known. The effect of food on the pharmacokinetics of the metformin component was indeterminate.

Glyburide

Single-dose studies with Micronase® tablets in normal subjects demonstrate significant absorption of glyburide within 1 hour, peak drug levels at about 4 hours, and low but detectable levels at 24 hours. Mean serum levels of glyburide, as reflected by areas under the serum concentration-time curve, increase in proportion to corresponding increases in dose. Bioequivalence has not been established between GLUCOVANCE and single-ingredient glyburide products.

Metformin Hydrochloride

The absolute bioavailability of a 500 mg metformin hydrochloride tablet given under fasting conditions is approximately 50% to 60%. Studies using single oral doses of metformin tablets of 500 mg and 1500 mg, and 850 mg to 2550 mg, indicate that there is a lack of dose proportionality with increasing doses, which is due to decreased absorption rather than an alteration in elimination. Food decreases the extent of and slightly delays the absorption of metformin, as shown by approximately a 40% lower peak concentration and a 25% lower AUC in plasma and a 35-minute prolongation of time to peak plasma concentration following administration of a single 850 mg tablet of metformin with food, compared to the same tablet strength administered fasting. The clinical relevance of these decreases is unknown.

Distribution

Glyburide

Sulfonylurea drugs are extensively bound to serum proteins. Displacement from protein binding sites by other drugs may lead to enhanced hypoglycemic action. In vitro, the protein binding exhibited by glyburide is predominantly non-ionic, whereas that of other sulfonylureas (chlorpropamide, tolbutamide, tolazamide) is predominantly ionic. Acidic drugs, such as phenylbutazone, warfarin, and salicylates, displace the ionic-binding sulfonylureas from serum proteins to a far greater extent than the non-ionic binding glyburide. It has not been shown that this difference in protein binding results in fewer drug-drug interactions with glyburide tablets in clinical use.

Metformin Hydrochloride

The apparent volume of distribution (V/F) of metformin following single oral doses of 850 mg averaged 654±358 L. Metformin is negligibly bound to plasma proteins. Metformin partitions into erythrocytes, most likely as a function of time. At usual clinical doses and dosing schedules of metformin, steady state plasma concentrations of metformin are reached within 24 to 48 hours and are generally <1 µg/mL. During controlled clinical trials, maximum metformin plasma levels did not exceed 5 µg/mL, even at maximum doses.

Metabolism and Elimination

Glyburide

The decrease of glyburide in the serum of normal healthy individuals is biphasic; the terminal half-life is about 10 hours. The major metabolite of glyburide is the 4-trans-hydroxy derivative. A second metabolite, the 3-cis-hydroxy derivative, also occurs. These metabolites probably contribute no significant hypoglycemic action in humans since they are only weakly active (1/400 and 1/40 as active, respectively, as glyburide) in rabbits. Glyburide is excreted as metabolites in the bile and urine, approximately 50% by each route. This dual excretory pathway is qualitatively different from that of other sulfonylureas, which are excreted primarily in the urine.

Metformin Hydrochloride

Intravenous single-dose studies in normal subjects demonstrate that metformin is excreted unchanged in the urine and does not undergo hepatic metabolism (no metabolites have been identified in humans) nor biliary excretion. Renal clearance (see Table 1) is approximately 3.5 times greater than creatinine clearance, which indicates that tubular secretion is the major route of metformin elimination. Following oral administration, approximately 90% of the absorbed drug is eliminated via the renal route within the first 24 hours, with a plasma elimination half-life of approximately 6.2 hours. In blood, the elimination half-life is approximately 17.6 hours, suggesting that the erythrocyte mass may be a compartment of distribution.

Special Populations

Patients With Type 2 Diabetes

Multiple-dose studies with glyburide in patients with type 2 diabetes demonstrate drug level concentration-time curves similar to single-dose studies, indicating no buildup of drug in tissue depots.

In the presence of normal renal function, there are no differences between single- or multiple-dose pharmacokinetics of metformin between patients with type 2 diabetes and normal subjects (see Table 1), nor is there any accumulation of metformin in either group at usual clinical doses.

Hepatic Insufficiency

No pharmacokinetic studies have been conducted in patients with hepatic insufficiency for either glyburide or metformin.

Renal Insufficiency

No information is available on the pharmacokinetics of glyburide in patients with renal insufficiency.

In patients with decreased renal function (based on creatinine clearance), the plasma and blood half-life of metformin is prolonged and the renal clearance is decreased in proportion to the decrease in creatinine clearance (see Table 1; also, see WARNINGS).

Geriatrics

There is no information on the pharmacokinetics of glyburide in elderly patients.

Limited data from controlled pharmacokinetic studies of metformin in healthy elderly subjects suggest that total plasma clearance is decreased, the half-life is prolonged, and Cmax is increased, when compared to healthy young subjects. From these data, it appears that the change in metformin pharmacokinetics with aging is primarily accounted for by a change in renal function (see Table 1). Metformin treatment should not be initiated in patients ≥80 years of age unless measurement of creatinine clearance demonstrates that renal function is not reduced.

Table 1: Select Mean (±SD) Metformin Pharmacokinetic Parameters Following Single or Multiple Oral Doses of Metformin
Subject Groups: Metformin Dosea (number of subjects) | Cmaxb (µg/mL) | Tmaxc (hrs) | Renal Clearance (mL/min)
Healthy, nondiabetic adults:
500 mg SDd (24) | 1.03 (±0.33) | 2.75 (±0.81) | 600 (±132)
850 mg SD (74)e | 1.60 (±0.38) | 2.64 (±0.82) | 552 (±139)
850 mg t.i.d. for 19 dosesf (9) | 2.01 (±0.42) | 1.79 (±0.94) | 642 (±173)
Adults with type 2 diabetes:
850 mg SD (23) | 1.48 (±0.5) | 3.32 (±1.08) | 491 (±138)
850 mg t.i.d. for 19 dosesf (9) | 1.90 (±0.62) | 2.01 (±1.22) | 550 (±160)
Elderlyg, healthy nondiabetic adults:
850 mg SD (12) | 2.45 (±0.70) | 2.71 (±1.05) | 412 (±98)
Renal-impaired adults: 850 mg SD
Mild (CLcrh 61-90 mL/min) (5) | 1.86 (±0.52) | 3.20 (±0.45) | 384 (±122)
Moderate (CLcr 31-60 mL/min) (4) | 4.12 (±1.83) | 3.75 (±0.50) | 108 (±57)
Severe (CLcr 10-30 mL/min) (6) | 3.93 (±0.92) | 4.01 (±1.10) | 130 (±90)
a All doses given fasting except the first 18 doses of the multiple-dose studies
b Peak plasma concentration
c Time to peak plasma concentration
d SD=single dose
e Combined results (average means) of 5 studies: mean age 32 years (range 23-59 years)
f Kinetic study done following dose 19, given fasting
g Elderly subjects, mean age 71 years (range 65-81 years)
h CLcr=creatinine clearance normalized to body surface area of 1.73 m^2

Pediatrics

After administration of a single oral GLUCOPHAGE® (metformin hydrochloride) 500 mg tablet with food, geometric mean metformin Cmax and AUC differed <5% between pediatric type 2 diabetic patients (12-16 years of age) and gender- and weight-matched healthy adults (20-45 years of age), all with normal renal function.

After administration of a single oral GLUCOVANCE tablet with food, dose-normalized geometric mean glyburide Cmax and AUC in pediatric patients with type 2 diabetes (11-16 years of age, n=28, mean body weight of 97 kg) differed <6% from historical values in healthy adults.

Gender

There is no information on the effect of gender on the pharmacokinetics of glyburide.

Metformin pharmacokinetic parameters did not differ significantly in subjects with or without type 2 diabetes when analyzed according to gender (males=19, females=16). Similarly, in controlled clinical studies in patients with type 2 diabetes, the antihyperglycemic effect of metformin was comparable in males and females.

Race

No information is available on race differences in the pharmacokinetics of glyburide.

No studies of metformin pharmacokinetic parameters according to race have been performed. In controlled clinical studies of metformin in patients with type 2 diabetes, the antihyperglycemic effect was comparable in whites (n=249), blacks (n=51), and Hispanics (n=24).

Clinical Studies

Patients with Inadequate Glycemic Control on Diet and Exercise Alone

In a 20-week, double-blind, multicenter U.S. clinical trial, a total of 806 drug-naive patients with type 2 diabetes, whose hyperglycemia was not adequately controlled with diet and exercise alone (baseline fasting plasma glucose [FPG] <240 mg/dL, baseline hemoglobin A1c [HbA1c] between 7% and 11%), were randomized to receive initial therapy with placebo, 2.5 mg glyburide, 500 mg metformin, GLUCOVANCE 1.25 mg/250 mg, or GLUCOVANCE 2.5 mg/500 mg. After 4 weeks, the dose was progressively increased (up to the 8-week visit) to a maximum of 4 tablets daily as needed to reach a target FPG of 126 mg/dL. Trial data at 20 weeks are summarized in Table 2.

Table 2: Placebo- and Active-Controlled Trial of GLUCOVANCE in Patients with Inadequate Glycemic Control on Diet and Exercise Alone: Summary of Trial Data at 20 Weeks
 | Placebo | Glyburide 2.5 mg tablets | Metformin 500 mg tablets | GLUCOVANCE 1.25 mg/250 mg tablets | GLUCOVANCE 2.5 mg/500 mg tablets
Mean Final Dose | 0 mg | 5.3 mg | 1317 mg | 2.78 mg/557 mg | 4.1 mg/824 mg
Hemoglobin A1c | N=147 | N=142 | N=141 | N=149 | N=152
Baseline Mean (%) | 8.14 | 8.14 | 8.23 | 8.22 | 8.20
Mean Change from Baseline | −0.21 | −1.24 | −1.03 | −1.48 | −1.53
Difference from Placebo |  | −1.02 | −0.82 | −1.26a | −1.31a
Difference from Glyburide |  |  |  | −0.24b | −0.29b
Difference from Metformin |  |  |  | −0.44b | −0.49b
Fasting Plasma Glucose | N=159 | N=158 | N=156 | N=153 | N=154
Baseline Mean FPG (mg/dL) | 177.2 | 178.9 | 175.1 | 178 | 176.6
Mean Change from Baseline | 4.6 | −35.7 | −21.2 | −41.5 | −40.1
Difference from Placebo |  | −40.3 | −25.8 | −46.1a | −44.7a
Difference from Glyburide |  |  |  | −5.8c | −4.5c
Difference from Metformin |  |  |  | −20.3c | −18.9c
Body Weight Mean Change from Baseline | −0.7 kg | +1.7 kg | −0.6 kg | +1.4 kg | +1.9 kg
Final HbA1c Distribution (%) | N=147 | N=142 | N=141 | N=149 | N=152
<7% | 19.7% | 59.9% | 50.4% | 66.4% | 71.7%
≥7% and <8% | 37.4% | 26.1% | 29.8% | 25.5% | 19.1%
≥8% | 42.9% | 14.1% | 19.9% | 8.1% | 9.2%
a p<0.001
b p<0.05
c p=NS

Treatment with GLUCOVANCE resulted in significantly greater reduction in HbA1c and postprandial plasma glucose (PPG) compared to glyburide, metformin, or placebo. Also, GLUCOVANCE therapy resulted in greater reduction in FPG compared to glyburide, metformin, or placebo, but the differences from glyburide and metformin did not reach statistical significance.

Changes in the lipid profile associated with GLUCOVANCE treatment were similar to those seen with glyburide, metformin, and placebo.

The double-blind, placebo-controlled trial described above restricted enrollment to patients with HbA1c <11% or FPG <240 mg/dL. Screened patients ineligible for the first trial because of HbA1c and/or FPG exceeding these limits were treated directly with GLUCOVANCE 2.5 mg/500 mg in an open-label, uncontrolled protocol. In this study, 3 out of 173 patients (1.7%) discontinued because of inadequate therapeutic response. Across the group of 144 patients who completed 26 weeks of treatment, mean HbA1c was reduced from a baseline of 10.6% to 7.1%. The mean baseline FPG was 283 mg/dL and reduced to 164 and 161 mg/dL after 2 and 26 weeks, respectively. The mean final titrated dose of GLUCOVANCE was 7.85 mg/1569 mg (equivalent to approximately 3 GLUCOVANCE 2.5 mg/500 mg tablets per day).

Patients with Inadequate Glycemic Control on Sulfonylurea Alone

In a 16-week, double-blind, active-controlled U.S. clinical trial, a total of 639 patients with type 2 diabetes not adequately controlled (mean baseline HbA1c 9.5%, mean baseline FPG 213 mg/dL) while being treated with at least one-half the maximum dose of a sulfonylurea (eg, glyburide 10 mg, glipizide 20 mg) were randomized to receive glyburide (fixed dose, 20 mg), metformin (500 mg), GLUCOVANCE 2.5 mg/500 mg, or GLUCOVANCE 5 mg/500 mg. The doses of metformin and GLUCOVANCE were titrated to a maximum of 4 tablets daily as needed to achieve FPG <140 mg/dL. Trial data at 16 weeks are summarized in Table 3.

Table 3: GLUCOVANCE in Patients with Inadequate Glycemic Control on Sulfonylurea Alone: Summary of Trial Data at 16 Weeks
 | Glyburide 5 mg tablets | Metformin 500 mg tablets | GLUCOVANCE 2.5 mg/500 mg tablets | GLUCOVANCE 5 mg/500 mg tablets
Mean Final Dose | 20 mg | 1840 mg | 8.8 mg/1760 mg | 17 mg/1740 mg
Hemoglobin A1c | N=158 | N=142 | N=154 | N=159
Baseline Mean (%) | 9.63 | 9.51 | 9.43 | 9.44
Final Mean | 9.61 | 9.82 | 7.92 | 7.91
Difference from Glyburide |  |  | −1.69a | −1.70a
Difference from Metformin |  |  | −1.90a | −1.91a
Fasting Plasma Glucose | N=163 | N=152 | N=160 | N=160
Baseline Mean (mg/dL) | 218.4 | 213.4 | 212.2 | 210.2
Final Mean | 221.0 | 233.8 | 169.6 | 161.1
Difference from Glyburide |  |  | −51.3a | −59.9a
Difference from Metformin |  |  | −64.2a | −72.7a
Body Weight Mean Change from Baseline | +0.43 kg | −2.76 kg | +0.75 kg | +0.47 kg
Final HbA1c Distribution (%) | N=158 | N=142 | N=154 | N=159
<7% | 2.5% | 2.8% | 24.7% | 22.6%
≥7% and <8% | 9.5% | 11.3% | 33.1% | 37.1%
≥8% | 88% | 85.9% | 42.2% | 40.3%
a p<0.001

After 16 weeks, there was no significant change in the mean HbA1c in patients randomized to glyburide or metformin therapy. Treatment with GLUCOVANCE at doses up to 20 mg/2000 mg per day resulted in significant lowering of HbA1c, FPG, and PPG from baseline compared to glyburide or metformin alone.

Addition of Thiazolidinediones to GLUCOVANCE Therapy

In a 24-week, double-blind, multicenter U.S. clinical trial, patients with type 2 diabetes not adequately controlled on current oral antihyperglycemic therapy (either monotherapy or combination therapy) were first switched to open label GLUCOVANCE 2.5 mg/500 mg tablets and titrated to a maximum daily dose of 10 mg/2000 mg. A total of 365 patients inadequately controlled (HbA1c >7.0% and ≤10%) after 10 to 12 weeks of a daily GLUCOVANCE dose of at least 7.5 mg/1500 mg were randomized to receive add-on therapy with rosiglitazone 4 mg or placebo once daily. After 8 weeks, the rosiglitazone dose was increased to a maximum of 8 mg daily as needed to reach a target mean daily glucose of 126 mg/dL or HbA1c <7%. Trial data at 24 weeks or the last prior visit are summarized in Table 4.

Table 4: Effects of Adding Rosiglitazone or Placebo in Patients Treated with GLUCOVANCE in a 24-Week Trial
 | Placebo + GLUCOVANCE | Rosiglitazone + GLUCOVANCE
Mean Final Dose GLUCOVANCE Rosiglitazone | 10 mg/1992 mg 0 mg | 9.6 mg/1914 mg 7.4 mg
Hemoglobin A1c | N=178 | N=177
Baseline Mean (%) | 8.09 | 8.14
Final Mean | 8.21 | 7.23
Difference from Placeboa |  | −1.02b
Fasting Plasma Glucose | N=181 | N=176
Baseline Mean (mg/dL) | 173.1 | 178.4
Final Mean | 181.4 | 136.3
Difference from Placeboa |  | −48.5b
Body Weight Mean Change from Baseline | +0.03 kg | +3.03 kg
Final HbA1c Distribution (%) | N=178 | N=177
<7% | 13.5% | 42.4%
≥7% and <8% | 32.0% | 38.4%
≥8% | 54.5% | 19.2%
a Adjusted for the baseline mean difference
b p<0.001

For patients who did not achieve adequate glycemic control on GLUCOVANCE, the addition of rosiglitazone, compared to placebo, resulted in significant lowering of HbA1c and FPG.

INDICATIONS AND USAGE

GLUCOVANCE (Glyburide and Metformin HCl) Tablets is indicated as an adjunct to diet and exercise to improve glycemic control in adults with type 2 diabetes mellitus.

CONTRAINDICATIONS

GLUCOVANCE is contraindicated in patients with:

1. Renal disease or renal dysfunction (eg, as suggested by serum creatinine levels ≥1.5 mg/dL [males], ≥1.4 mg/dL [females], or abnormal creatinine clearance) which may also result from conditions such as cardiovascular collapse (shock), acute myocardial infarction, and septicemia (see WARNINGS and PRECAUTIONS).
2. Known hypersensitivity to metformin hydrochloride or glyburide.
3. Acute or chronic metabolic acidosis, including diabetic ketoacidosis, with or without coma. Diabetic ketoacidosis should be treated with insulin.

GLUCOVANCE should be temporarily discontinued in patients undergoing radiologic studies involving intravascular administration of iodinated contrast materials, because use of such products may result in acute alteration of renal function. (See also PRECAUTIONS.)

WARNINGS

Metformin Hydrochloride

BOXED WARNING

Lactic acidosis:

Lactic acidosis is a rare, but serious, metabolic complication that can occur due to metformin accumulation during treatment with GLUCOVANCE (Glyburide and Metformin HCl) Tablets; when it occurs, it is fatal in approximately 50% of cases. Lactic acidosis may also occur in association with a number of pathophysiologic conditions, including diabetes mellitus, and whenever there is significant tissue hypoperfusion and hypoxemia. Lactic acidosis is characterized by elevated blood lactate levels (>5 mmol/L), decreased blood pH, electrolyte disturbances with an increased anion gap, and an increased lactate/pyruvate ratio. When metformin is implicated as the cause of lactic acidosis, metformin plasma levels >5 µg/mL are generally found.

The reported incidence of lactic acidosis in patients receiving metformin hydrochloride is very low (approximately 0.03 cases/1000 patient-years, with approximately 0.015 fatal cases/1000 patient-years). In more than 20,000 patient-years exposure to metformin in clinical trials, there were no reports of lactic acidosis. Reported cases have occurred primarily in diabetic patients with significant renal insufficiency, including both intrinsic renal disease and renal hypoperfusion, often in the setting of multiple concomitant medical/surgical problems and multiple concomitant medications. Patients with congestive heart failure requiring pharmacologic management, in particular those with unstable or acute congestive heart failure who are at risk of hypoperfusion and hypoxemia, are at increased risk of lactic acidosis. The risk of lactic acidosis increases with the degree of renal dysfunction and the patient's age. The risk of lactic acidosis may, therefore, be significantly decreased by regular monitoring of renal function in patients taking metformin and by use of the minimum effective dose of metformin. In particular, treatment of the elderly should be accompanied by careful monitoring of renal function. GLUCOVANCE treatment should not be initiated in patients ≥80 years of age unless measurement of creatinine clearance demonstrates that renal function is not reduced, as these patients are more susceptible to developing lactic acidosis. In addition, GLUCOVANCE should be promptly withheld in the presence of any condition associated with hypoxemia, dehydration, or sepsis. Because impaired hepatic function may significantly limit the ability to clear lactate, GLUCOVANCE should generally be avoided in patients with clinical or laboratory evidence of hepatic disease. Patients should be cautioned against excessive alcohol intake, either acute or chronic, when taking GLUCOVANCE, since alcohol potentiates the effects of metformin hydrochloride on lactate metabolism. In addition, GLUCOVANCE should be temporarily discontinued prior to any intravascular radiocontrast study and for any surgical procedure (see also PRECAUTIONS).

The onset of lactic acidosis often is subtle, and accompanied only by nonspecific symptoms such as malaise, myalgias, respiratory distress, increasing somnolence, and nonspecific abdominal distress. There may be associated hypothermia, hypotension, and resistant bradyarrhythmias with more marked acidosis. The patient and the patient's physician must be aware of the possible importance of such symptoms and the patient should be instructed to notify the physician immediately if they occur (see also PRECAUTIONS). GLUCOVANCE should be withdrawn until the situation is clarified. Serum electrolytes, ketones, blood glucose, and if indicated, blood pH, lactate levels, and even blood metformin levels may be useful. Once a patient is stabilized on any dose level of GLUCOVANCE, gastrointestinal symptoms, which are common during initiation of therapy with metformin, are unlikely to be drug related. Later occurrence of gastrointestinal symptoms could be due to lactic acidosis or other serious disease.

Levels of fasting venous plasma lactate above the upper limit of normal but less than 5 mmol/L in patients taking GLUCOVANCE do not necessarily indicate impending lactic acidosis and may be explainable by other mechanisms, such as poorly controlled diabetes or obesity, vigorous physical activity, or technical problems in sample handling. (See also PRECAUTIONS.)

Lactic acidosis should be suspected in any diabetic patient with metabolic acidosis lacking evidence of ketoacidosis (ketonuria and ketonemia).

Lactic acidosis is a medical emergency that must be treated in a hospital setting. In a patient with lactic acidosis who is taking GLUCOVANCE, the drug should be discontinued immediately and general supportive measures promptly instituted. Because metformin hydrochloride is dialyzable (with a clearance of up to 170 mL/min under good hemodynamic conditions), prompt hemodialysis is recommended to correct the acidosis and remove the accumulated metformin. Such management often results in prompt reversal of symptoms and recovery. (See also CONTRAINDICATIONS and PRECAUTIONS.)

SPECIAL WARNING ON INCREASED RISK OF CARDIOVASCULAR MORTALITY

The administration of oral hypoglycemic drugs has been reported to be associated with increased cardiovascular mortality as compared to treatment with diet alone or diet plus insulin. This warning is based on the study conducted by the University Group Diabetes Program (UGDP), a long-term prospective clinical trial designed to evaluate the effectiveness of glucose-lowering drugs in preventing or delaying vascular complications in patients with non-insulin-dependent diabetes. The study involved 823 patients who were randomly assigned to 1 of 4 treatment groups (Diabetes 19 (Suppl. 2):747-830, 1970).

UGDP reported that patients treated for 5 to 8 years with diet plus a fixed dose of tolbutamide (1.5 g per day) had a rate of cardiovascular mortality approximately 2½ times that of patients treated with diet alone. A significant increase in total mortality was not observed, but the use of tolbutamide was discontinued based on the increase in cardiovascular mortality, thus limiting the opportunity for the study to show an increase in overall mortality. Despite controversy regarding the interpretation of these results, the findings of the UGDP study provide an adequate basis for this warning. The patient should be informed of the potential risks and benefits of glyburide and of alternative modes of therapy.

Although only 1 drug in the sulfonylurea class (tolbutamide) was included in this study, it is prudent from a safety standpoint to consider that this warning may also apply to other hypoglycemic drugs in this class, in view of their close similarities in mode of action and chemical structure.

PRECAUTIONS

General

Macrovascular Outcomes

There have been no clinical studies establishing conclusive evidence of macrovascular risk reduction with GLUCOVANCE or any other antidiabetic drug.

GLUCOVANCE

Hypoglycemia

GLUCOVANCE is capable of producing hypoglycemia or hypoglycemic symptoms, therefore, proper patient selection, dosing, and instructions are important to avoid potential hypoglycemic episodes. The risk of hypoglycemia is increased when caloric intake is deficient, when strenuous exercise is not compensated by caloric supplementation, or during concomitant use with other glucose-lowering agents or ethanol. Renal or hepatic insufficiency may cause elevated drug levels of both glyburide and metformin hydrochloride, and the hepatic insufficiency may also diminish gluconeogenic capacity, both of which increase the risk of hypoglycemic reactions. Elderly, debilitated, or malnourished patients and those with adrenal or pituitary insufficiency or alcohol intoxication are particularly susceptible to hypoglycemic effects. Hypoglycemia may be difficult to recognize in the elderly and people who are taking beta-adrenergic blocking drugs.

Glyburide

Hemolytic anemia

Treatment of patients with glucose-6-phosphate dehydrogenase (G6PD) deficiency with sulfonylurea agents can lead to hemolytic anemia. Because GLUCOVANCE belongs to the class of sulfonylurea agents, caution should be used in patients with G6PD deficiency and a non-sulfonylurea alternative should be considered. In postmarketing reports, hemolytic anemia has also been reported in patients who did not have known G6PD deficiency.

Metformin Hydrochloride

Monitoring of renal function

Metformin is known to be substantially excreted by the kidney, and the risk of metformin accumulation and lactic acidosis increases with the degree of impairment of renal function. Thus, patients with serum creatinine levels above the upper limit of normal for their age should not receive GLUCOVANCE. In patients with advanced age, GLUCOVANCE should be carefully titrated to establish the minimum dose for adequate glycemic effect, because aging is associated with reduced renal function. In elderly patients, particularly those ≥80 years of age, renal function should be monitored regularly and, generally, GLUCOVANCE should not be titrated to the maximum dose (see WARNINGS and DOSAGE AND ADMINISTRATION). Before initiation of GLUCOVANCE therapy and at least annually thereafter, renal function should be assessed and verified as normal. In patients in whom development of renal dysfunction is anticipated, renal function should be assessed more frequently and GLUCOVANCE discontinued if evidence of renal impairment is present.

Use of concomitant medications that may affect renal function or metformin disposition

Concomitant medication(s) that may affect renal function or result in significant hemodynamic change or may interfere with the disposition of metformin, such as cationic drugs that are eliminated by renal tubular secretion (see PRECAUTIONS: Drug Interactions), should be used with caution.

Radiologic studies involving the use of intravascular iodinated contrast materials (for example, intravenous urogram, intravenous cholangiography, angiography, and computed tomography (CT) scans with intravascular contrast materials)

Intravascular contrast studies with iodinated materials can lead to acute alteration of renal function and have been associated with lactic acidosis in patients receiving metformin (see CONTRAINDICATIONS). Therefore, in patients in whom any such study is planned, GLUCOVANCE should be temporarily discontinued at the time of or prior to the procedure, and withheld for 48 hours subsequent to the procedure and reinstituted only after renal function has been reevaluated and found to be normal.

Hypoxic states

Cardiovascular collapse (shock) from whatever cause, acute congestive heart failure, acute myocardial infarction, and other conditions characterized by hypoxemia have been associated with lactic acidosis and may also cause prerenal azotemia. When such events occur in patients on GLUCOVANCE therapy, the drug should be promptly discontinued.

Surgical procedures

GLUCOVANCE therapy should be temporarily suspended for any surgical procedure (except minor procedures not associated with restricted intake of food and fluids) and should not be restarted until the patient's oral intake has resumed and renal function has been evaluated as normal.

Alcohol intake

Alcohol is known to potentiate the effect of metformin on lactate metabolism. Patients, therefore, should be warned against excessive alcohol intake, acute or chronic, while receiving GLUCOVANCE. Due to its effect on the gluconeogenic capacity of the liver, alcohol may also increase the risk of hypoglycemia.

Impaired hepatic function

Since impaired hepatic function has been associated with some cases of lactic acidosis, GLUCOVANCE should generally be avoided in patients with clinical or laboratory evidence of hepatic disease.

Vitamin B12 levels

In controlled clinical trials with metformin of 29 weeks duration, a decrease to subnormal levels of previously normal serum vitamin B12, without clinical manifestations, was observed in approximately 7% of patients. Such decrease, possibly due to interference with B12 absorption from the B12-intrinsic factor complex is, however, very rarely associated with anemia and appears to be rapidly reversible with discontinuation of metformin or vitamin B12 supplementation. Measurement of hematologic parameters on an annual basis is advised in patients on metformin and any apparent abnormalities should be appropriately investigated and managed (see PRECAUTIONS: Laboratory Tests).

Certain individuals (those with inadequate vitamin B12 or calcium intake or absorption) appear to be predisposed to developing subnormal vitamin B12 levels. In these patients, routine serum vitamin B12 measurements at 2- to 3-year intervals may be useful.

Change in clinical status of patients with previously controlled type 2 diabetes

A patient with type 2 diabetes previously well controlled on metformin who develops laboratory abnormalities or clinical illness (especially vague and poorly defined illness) should be evaluated promptly for evidence of ketoacidosis or lactic acidosis. Evaluation should include serum electrolytes and ketones, blood glucose and, if indicated, blood pH, lactate, pyruvate, and metformin levels. If acidosis of either form occurs, GLUCOVANCE must be stopped immediately and other appropriate corrective measures initiated (see also WARNINGS).

Addition of Thiazolidinediones to GLUCOVANCE Therapy

Hypoglycemia

Patients receiving GLUCOVANCE in combination with a thiazolidinedione may be at risk for hypoglycemia.

Weight gain

Weight gain was seen with the addition of rosiglitazone to GLUCOVANCE, similar to that reported for thiazolidinedione therapy alone.

Hepatic effects

When a thiazolidinedione is used in combination with GLUCOVANCE, periodic monitoring of liver function tests should be performed in compliance with the labeled recommendations for the thiazolidinedione.

Information for Patients

GLUCOVANCE

Patients should be informed of the potential risks and benefits of GLUCOVANCE and alternative modes of therapy. They should also be informed about the importance of adherence to dietary instructions; a regular exercise program; and regular testing of blood glucose, glycosylated hemoglobin, renal function, and hematologic parameters.

The risks of lactic acidosis associated with metformin therapy, its symptoms, and conditions that predispose to its development, as noted in the WARNINGS and PRECAUTIONS sections, should be explained to patients. Patients should be advised to discontinue GLUCOVANCE immediately and promptly notify their health practitioner if unexplained hyperventilation, myalgia, malaise, unusual somnolence, or other nonspecific symptoms occur. Once a patient is stabilized on any dose level of GLUCOVANCE, gastrointestinal symptoms, which are common during initiation of metformin therapy, are unlikely to be drug related. Later occurrence of gastrointestinal symptoms could be due to lactic acidosis or other serious disease.

The risks of hypoglycemia, its symptoms and treatment, and conditions that predispose to its development should be explained to patients and responsible family members.

Patients should be counseled against excessive alcohol intake, either acute or chronic, while receiving GLUCOVANCE. (See Patient Information printed below.)

Laboratory Tests

Periodic fasting blood glucose (FBG) and HbA1c measurements should be performed to monitor therapeutic response.

Initial and periodic monitoring of hematologic parameters (eg, hemoglobin/hematocrit and red blood cell indices) and renal function (serum creatinine) should be performed, at least on an annual basis. While megaloblastic anemia has rarely been seen with metformin therapy, if this is suspected, vitamin B12 deficiency should be excluded.

Drug Interactions

GLUCOVANCE

Certain drugs tend to produce hyperglycemia and may lead to loss of blood glucose control. These drugs include thiazides and other diuretics, corticosteroids, phenothiazines, thyroid products, estrogens, oral contraceptives, phenytoin, nicotinic acid, sympathomimetics, calcium channel blocking drugs, and isoniazid. When such drugs are administered to a patient receiving GLUCOVANCE, the patient should be closely observed for loss of blood glucose control. When such drugs are withdrawn from a patient receiving GLUCOVANCE, the patient should be observed closely for hypoglycemia. Metformin is negligibly bound to plasma proteins and is, therefore, less likely to interact with highly protein-bound drugs such as salicylates, sulfonamides, chloramphenicol, and probenecid as compared to sulfonylureas, which are extensively bound to serum proteins.

Glyburide

The hypoglycemic action of sulfonylureas may be potentiated by certain drugs, including nonsteroidal anti-inflammatory agents and other drugs that are highly protein bound, salicylates, sulfonamides, chloramphenicol, probenecid, coumarins, monoamine oxidase inhibitors, and beta-adrenergic blocking agents. When such drugs are administered to a patient receiving GLUCOVANCE, the patient should be observed closely for hypoglycemia. When such drugs are withdrawn from a patient receiving GLUCOVANCE, the patient should be observed closely for loss of blood glucose control.

A possible interaction between glyburide and ciprofloxacin, a fluoroquinolone antibiotic, has been reported, resulting in a potentiation of the hypoglycemic action of glyburide. The mechanism for this interaction is not known.

A potential interaction between oral miconazole and oral hypoglycemic agents leading to severe hypoglycemia has been reported. Whether this interaction also occurs with the intravenous, topical, or vaginal preparations of miconazole is not known.

Metformin Hydrochloride

Furosemide

A single-dose, metformin-furosemide drug interaction study in healthy subjects demonstrated that pharmacokinetic parameters of both compounds were affected by coadministration. Furosemide increased the metformin plasma and blood Cmax by 22% and blood AUC by 15%, without any significant change in metformin renal clearance. When administered with metformin, the Cmax and AUC of furosemide were 31% and 12% smaller, respectively, than when administered alone, and the terminal half-life was decreased by 32%, without any significant change in furosemide renal clearance. No information is available about the interaction of metformin and furosemide when coadministered chronically.

Nifedipine

A single-dose, metformin-nifedipine drug interaction study in normal healthy volunteers demonstrated that coadministration of nifedipine increased plasma metformin Cmax and AUC by 20% and 9%, respectively, and increased the amount excreted in the urine. Tmax and half-life were unaffected. Nifedipine appears to enhance the absorption of metformin. Metformin had minimal effects on nifedipine.

Cationic drugs

Cationic drugs (eg, amiloride, digoxin, morphine, procainamide, quinidine, quinine, ranitidine, triamterene, trimethoprim, or vancomycin) that are eliminated by renal tubular secretion theoretically have the potential for interaction with metformin by competing for common renal tubular transport systems. Such interaction between metformin and oral cimetidine has been observed in normal healthy volunteers in both single- and multiple-dose, metformin-cimetidine drug interaction studies, with a 60% increase in peak metformin plasma and whole blood concentrations and a 40% increase in plasma and whole blood metformin AUC. There was no change in elimination half-life in the single-dose study. Metformin had no effect on cimetidine pharmacokinetics. Although such interactions remain theoretical (except for cimetidine), careful patient monitoring and dose adjustment of GLUCOVANCE and/or the interfering drug is recommended in patients who are taking cationic medications that are excreted via the proximal renal tubular secretory system.

Other

In healthy volunteers, the pharmacokinetics of metformin and propranolol and metformin and ibuprofen were not affected when coadministered in single-dose interaction studies.

Carcinogenesis, Mutagenesis, Impairment of Fertility

No animal studies have been conducted with the combined products in GLUCOVANCE. The following data are based on findings in studies performed with the individual products.

Glyburide

Studies in rats with glyburide alone at doses up to 300 mg/kg/day (approximately 145 times the maximum recommended human daily [MRHD] dose of 20 mg for the glyburide component of GLUCOVANCE based on body surface area comparisons) for 18 months revealed no carcinogenic effects. In a 2-year oncogenicity study of glyburide in mice, there was no evidence of treatment-related tumors.

There was no evidence of mutagenic potential of glyburide alone in the following in vitro tests: Salmonella microsome test (Ames test) and in the DNA damage/alkaline elution assay.

Metformin Hydrochloride

Long-term carcinogenicity studies were performed with metformin alone in rats (dosing duration of 104 weeks) and mice (dosing duration of 91 weeks) at doses up to and including 900 mg/kg/day and 1500 mg/kg/day, respectively. These doses are both approximately 4 times the MRHD dose of 2000 mg of the metformin component of GLUCOVANCE based on body surface area comparisons. No evidence of carcinogenicity with metformin alone was found in either male or female mice. Similarly, there was no tumorigenic potential observed with metformin alone in male rats. There was, however, an increased incidence of benign stromal uterine polyps in female rats treated with 900 mg/kg/day of metformin alone.

There was no evidence of a mutagenic potential of metformin alone in the following in vitro tests: Ames test (S. typhimurium), gene mutation test (mouse lymphoma cells), or chromosomal aberrations test (human lymphocytes). Results in the in vivo mouse micronucleus test were also negative.

Fertility of male or female rats was unaffected by metformin alone when administered at doses as high as 600 mg/kg/day, which is approximately 3 times the MRHD dose of the metformin component of GLUCOVANCE based on body surface area comparisons.

Pregnancy

Teratogenic Effects: Pregnancy Category B

Recent information strongly suggests that abnormal blood glucose levels during pregnancy are associated with a higher incidence of congenital abnormalities. Most experts recommend that insulin be used during pregnancy to maintain blood glucose as close to normal as possible. Because animal reproduction studies are not always predictive of human response, GLUCOVANCE should not be used during pregnancy unless clearly needed. (See below.)

There are no adequate and well-controlled studies in pregnant women with GLUCOVANCE or its individual components. No animal studies have been conducted with the combined products in GLUCOVANCE. The following data are based on findings in studies performed with the individual products.

Glyburide

Reproduction studies were performed in rats and rabbits at doses up to 500 times the MRHD dose of 20 mg of the glyburide component of GLUCOVANCE based on body surface area comparisons and revealed no evidence of impaired fertility or harm to the fetus due to glyburide.

Metformin Hydrochloride

Metformin alone was not teratogenic in rats or rabbits at doses up to 600 mg/kg/day. This represents an exposure of about 2 and 6 times the MRHD dose of 2000 mg of the metformin component of GLUCOVANCE based on body surface area comparisons for rats and rabbits, respectively. Determination of fetal concentrations demonstrated a partial placental barrier to metformin.

Nonteratogenic Effects

Prolonged severe hypoglycemia (4-10 days) has been reported in neonates born to mothers who were receiving a sulfonylurea drug at the time of delivery. This has been reported more frequently with the use of agents with prolonged half-lives. It is not recommended that GLUCOVANCE be used during pregnancy. However, if it is used, GLUCOVANCE should be discontinued at least 2 weeks before the expected delivery date. (See Pregnancy: Teratogenic Effects: Pregnancy Category B.)

Nursing Mothers

Although it is not known whether glyburide is excreted in human milk, some sulfonylurea drugs are known to be excreted in human milk. Studies in lactating rats show that metformin is excreted into milk and reaches levels comparable to those in plasma. Similar studies have not been conducted in nursing mothers. Because the potential for hypoglycemia in nursing infants may exist, a decision should be made whether to discontinue nursing or to discontinue GLUCOVANCE, taking into account the importance of the drug to the mother. If GLUCOVANCE is discontinued, and if diet alone is inadequate for controlling blood glucose, insulin therapy should be considered.

Pediatric Use

The safety and efficacy of GLUCOVANCE were evaluated in an active-controlled, double-blind, 26-week randomized trial involving a total of 167 pediatric patients (ranging from 9-16 years of age) with type 2 diabetes. GLUCOVANCE was not shown statistically to be superior to either metformin or glyburide with respect to reducing HbA1c from baseline (see Table 5). No unexpected safety findings were associated with GLUCOVANCE in this trial.

Table 5: HbA1c (Percent) Change From Baseline at 26 Weeks: Pediatric Study
 | Glyburide 2.5 mg tablets | Metformin 500 mg tablets | GLUCOVANCE 1.25 mg/250 mg tablets
Mean Final Dose | 6.5 mg | 1500 mg | 3.1 mg/623 mg
Hemoglobin A1c | N=49 | N=54 | N=57
Baseline Mean (%) | 7.70 | 7.99 | 7.85
Mean Change from Baseline | −0.96 | −0.48 | −0.80
Difference from Metformin |  |  | −0.32
Difference from Glyburide |  |  | +0.16

Geriatric Use

Of the 642 patients who received GLUCOVANCE in double-blind clinical studies, 23.8% were 65 and older while 2.8% were 75 and older. Of the 1302 patients who received GLUCOVANCE in open-label clinical studies, 20.7% were 65 and older while 2.5% were 75 and older. No overall differences in effectiveness or safety were observed between these patients and younger patients, and other reported clinical experience has not identified differences in response between the elderly and younger patients, but greater sensitivity of some older individuals cannot be ruled out.

Metformin hydrochloride is known to be substantially excreted by the kidney and because the risk of serious adverse reactions to the drug is greater in patients with impaired renal function, GLUCOVANCE should only be used in patients with normal renal function (see CONTRAINDICATIONS, WARNINGS, and CLINICAL PHARMACOLOGY: Pharmacokinetics). Because aging is associated with reduced renal function, GLUCOVANCE should be used with caution as age increases. Care should be taken in dose selection and should be based on careful and regular monitoring of renal function. Generally, elderly patients should not be titrated to the maximum dose of GLUCOVANCE (see also WARNINGS and DOSAGE AND ADMINISTRATION).

ADVERSE REACTIONS

GLUCOVANCE

In double-blind clinical trials involving GLUCOVANCE as initial therapy or as second-line therapy, a total of 642 patients received GLUCOVANCE, 312 received metformin therapy, 324 received glyburide therapy, and 161 received placebo. The percent of patients reporting events and types of adverse events reported in clinical trials of GLUCOVANCE (all strengths) as initial therapy and second-line therapy are listed in Table 6.

Table 6: Most Common Clinical Adverse Events (>5%) in Double-Blind Clinical Studies of GLUCOVANCE Used as Initial or Second-Line Therapy
Adverse Event | Number (%) of Patients
Adverse Event | Placebo N=161 | Glyburide N=324 | Metformin N=312 | GLUCOVANCE N=642
Upper respiratory infection | 22 (13.7) | 57 (17.6) | 51 (16.3) | 111 (17.3)
Diarrhea | 9 (5.6) | 20 (6.2) | 64 (20.5) | 109 (17.0)
Headache | 17 (10.6) | 37 (11.4) | 29 (9.3) | 57 (8.9)
Nausea/vomiting | 10 (6.2) | 17 (5.2) | 38 (12.2) | 49 (7.6)
Abdominal pain | 6 (3.7) | 10 (3.1) | 25 (8.0) | 44 (6.9)
Dizziness | 7 (4.3) | 18 (5.6) | 12 (3.8) | 35 (5.5)

In a controlled clinical trial of rosiglitazone versus placebo in patients treated with GLUCOVANCE (n=365), 181 patients received GLUCOVANCE with rosiglitazone and 184 received GLUCOVANCE with placebo.

Edema was reported in 7.7% (14/181) of patients treated with rosiglitazone compared to 2.2% (4/184) of patients treated with placebo. A mean weight gain of 3 kg was observed in rosiglitazone-treated patients.

Disulfiram-like reactions have very rarely been reported in patients treated with glyburide tablets.

Hypoglycemia

In controlled clinical trials of GLUCOVANCE there were no hypoglycemic episodes requiring medical intervention and/or pharmacologic therapy; all events were managed by the patients. The incidence of reported symptoms of hypoglycemia (such as dizziness, shakiness, sweating, and hunger), in the initial therapy trial of GLUCOVANCE are summarized in Table 7. The frequency of hypoglycemic symptoms in patients treated with GLUCOVANCE 1.25 mg/250 mg was highest in patients with a baseline HbA1c <7%, lower in those with a baseline HbA1c of between 7% and 8%, and was comparable to placebo and metformin in those with a baseline HbA1c >8%. For patients with a baseline HbA1c between 8% and 11% treated with GLUCOVANCE 2.5 mg/500 mg as initial therapy, the frequency of hypoglycemic symptoms was 30% to 35%. As second-line therapy in patients inadequately controlled on sulfonylurea alone, approximately 6.8% of all patients treated with GLUCOVANCE experienced hypoglycemic symptoms. When rosiglitazone was added to GLUCOVANCE therapy, 22% of patients reported 1 or more fingerstick glucose measurements ≤50 mg/dL compared to 3.3% of placebo-treated patients. All hypoglycemic events were managed by the patients and only 1 patient discontinued for hypoglycemia. (See PRECAUTIONS: General: Addition of Thiazolidinediones to GLUCOVANCE Therapy.)

Gastrointestinal Reactions

The incidence of gastrointestinal (GI) side effects (diarrhea, nausea/vomiting, and abdominal pain) in the initial therapy trial are summarized in Table 7. Across all GLUCOVANCE trials, GI symptoms were the most common adverse events with GLUCOVANCE and were more frequent at higher dose levels. In controlled trials, <2% of patients discontinued GLUCOVANCE therapy due to GI adverse events.

Table 7: Treatment Emergent Symptoms of Hypoglycemia or Gastrointestinal Adverse Events in a Placebo- and Active-Controlled Trial of GLUCOVANCE as Initial Therapy
Variable | Placebo N=161 | Glyburide Tablets N=160 | Metformin Tablets N=159 | GLUCOVANCE 1.25 mg/250 mg Tablets N=158 | GLUCOVANCE 2.5 mg/500 mg Tablets N=162
Mean Final Dose | 0 mg | 5.3 mg | 1317 mg | 2.78 mg/557 mg | 4.1 mg/824 mg
Number (%) of patients with symptoms of hypoglycemia | 5 (3.1) | 34 (21.3) | 5 (3.1) | 18 (11.4) | 61 (37.7)
Number (%) of patients with gastrointestinal adverse events | 39 (24.2) | 38 (23.8) | 69 (43.3) | 50 (31.6) | 62 (38.3)

In postmarketing reports cholestatic jaundice and hepatitis may occur rarely which may progress to liver failure; GLUCOVANCE should be discontinued if this occurs.

OVERDOSAGE

Glyburide

Overdosage of sulfonylureas, including glyburide tablets, can produce hypoglycemia. Mild hypoglycemic symptoms, without loss of consciousness or neurological findings, should be treated aggressively with oral glucose and adjustments in drug dosage and/or meal patterns. Close monitoring should continue until the physician is assured that the patient is out of danger. Severe hypoglycemic reactions with coma, seizure, or other neurological impairment occur infrequently, but constitute medical emergencies requiring immediate hospitalization. If hypoglycemic coma is diagnosed or suspected, the patient should be given a rapid intravenous injection of concentrated (50%) glucose solution. This should be followed by a continuous infusion of a more dilute (10%) glucose solution at a rate that will maintain the blood glucose at a level above 100 mg/dL. Patients should be closely monitored for a minimum of 24 to 48 hours, since hypoglycemia may recur after apparent clinical recovery.

Metformin Hydrochloride

Overdose of metformin hydrochloride has occurred, including ingestion of amounts >50 g. Hypoglycemia was reported in approximately 10% of cases, but no causal association with metformin hydrochloride has been established. Lactic acidosis has been reported in approximately 32% of metformin overdose cases (see WARNINGS). Metformin is dialyzable with a clearance of up to 170 mL/min under good hemodynamic conditions. Therefore, hemodialysis may be useful for removal of accumulated drug from patients in whom metformin overdosage is suspected.

DOSAGE AND ADMINISTRATION

General Considerations

Dosage of GLUCOVANCE must be individualized on the basis of both effectiveness and tolerance while not exceeding the maximum recommended daily dose of 20 mg glyburide/2000 mg metformin. GLUCOVANCE should be given with meals and should be initiated at a low dose, with gradual dose escalation as described below, in order to avoid hypoglycemia (largely due to glyburide), reduce GI side effects (largely due to metformin), and permit determination of the minimum effective dose for adequate control of blood glucose for the individual patient.

With initial treatment and during dose titration, appropriate blood glucose monitoring should be used to determine the therapeutic response to GLUCOVANCE and to identify the minimum effective dose for the patient. Thereafter, HbA1c should be measured at intervals of approximately 3 months to assess the effectiveness of therapy. The therapeutic goal in all patients with type 2 diabetes is to decrease FPG, PPG, and HbA1c to normal or as near normal as possible. Ideally, the response to therapy should be evaluated using HbA1c (glycosylated hemoglobin), which is a better indicator of long-term glycemic control than FPG alone.

No studies have been performed specifically examining the safety and efficacy of switching to GLUCOVANCE therapy in patients taking concomitant glyburide (or other sulfonylurea) plus metformin. Changes in glycemic control may occur in such patients, with either hyperglycemia or hypoglycemia possible. Any change in therapy of type 2 diabetes should be undertaken with care and appropriate monitoring.

GLUCOVANCE in Patients with Inadequate Glycemic Control on Diet and Exercise

Recommended starting dose: 1.25 mg/250 mg once or twice daily with meals.

For patients with type 2 diabetes whose hyperglycemia cannot be satisfactorily managed with diet and exercise alone, the recommended starting dose of GLUCOVANCE is 1.25 mg/250 mg once a day with a meal. As initial therapy in patients with baseline HbA1c >9% or an FPG >200 mg/dL, a starting dose of GLUCOVANCE 1.25 mg/250 mg twice daily with the morning and evening meals may be used. Dosage increases should be made in increments of 1.25 mg/250 mg per day every 2 weeks up to the minimum effective dose necessary to achieve adequate control of blood glucose. In clinical trials of GLUCOVANCE as initial therapy, there was no experience with total daily doses >10 mg/2000 mg per day. GLUCOVANCE 5 mg/500 mg should not be used as initial therapy due to an increased risk of hypoglycemia.

GLUCOVANCE Use in Patients with Inadequate Glycemic Control on a Sulfonylurea and/or Metformin

Recommended starting dose: 2.5 mg/500 mg or 5 mg/500 mg twice daily with meals.

For patients not adequately controlled on either glyburide (or another sulfonylurea) or metformin alone, the recommended starting dose of GLUCOVANCE is 2.5 mg/500 mg or 5 mg/500 mg twice daily with the morning and evening meals. In order to avoid hypoglycemia, the starting dose of GLUCOVANCE should not exceed the daily doses of glyburide or metformin already being taken. The daily dose should be titrated in increments of no more than 5 mg/500 mg up to the minimum effective dose to achieve adequate control of blood glucose or to a maximum dose of 20 mg/2000 mg per day.

For patients previously treated with combination therapy of glyburide (or another sulfonylurea) plus metformin, if switched to GLUCOVANCE, the starting dose should not exceed the daily dose of glyburide (or equivalent dose of another sulfonylurea) and metformin already being taken. Patients should be monitored closely for signs and symptoms of hypoglycemia following such a switch and the dose of GLUCOVANCE should be titrated as described above to achieve adequate control of blood glucose.

Addition of Thiazolidinediones to GLUCOVANCE Therapy

For patients not adequately controlled on GLUCOVANCE, a thiazolidinedione can be added to GLUCOVANCE therapy. When a thiazolidinedione is added to GLUCOVANCE therapy, the current dose of GLUCOVANCE can be continued and the thiazolidinedione initiated at its recommended starting dose. For patients needing additional glycemic control, the dose of the thiazolidinedione can be increased based on its recommended titration schedule. The increased glycemic control attainable with GLUCOVANCE plus a thiazolidinedione may increase the potential for hypoglycemia at any time of day. In patients who develop hypoglycemia when receiving GLUCOVANCE and a thiazolidinedione, consideration should be given to reducing the dose of the glyburide component of GLUCOVANCE. As clinically warranted, adjustment of the dosages of the other components of the antidiabetic regimen should also be considered.

Specific Patient Populations

GLUCOVANCE is not recommended for use during pregnancy. The initial and maintenance dosing of GLUCOVANCE should be conservative in patients with advanced age, due to the potential for decreased renal function in this population. Any dosage adjustment requires a careful assessment of renal function. Generally, elderly, debilitated, and malnourished patients should not be titrated to the maximum dose of GLUCOVANCE to avoid the risk of hypoglycemia. Monitoring of renal function is necessary to aid in prevention of metformin-associated lactic acidosis, particularly in the elderly. (See WARNINGS.)

HOW SUPPLIED

GLUCOVANCE® (Glyburide and Metformin HCl) Tablets

GLUCOVANCE 2.5 mg/500 mg tablet is a pale orange, capsule-shaped, bevel-edged, biconvex, film-coated tablet with "BMS" debossed on one side and "6073" debossed on the opposite side.

GLUCOVANCE
Glyburide (mg) | Metformin hydrochloride (mg) | Bottle of 100
2.5 | 500 | NDC 54868-4609-1

STORAGE

Store at temperatures up to 25°C (77°F). [See USP Controlled Room Temperature.]

Dispense in light-resistant containers.

GLUCOVANCE® is a registered trademark of Merck Santé S.A.S., an associate of Merck KGaA of Darmstadt, Germany. Licensed to Bristol-Myers Squibb Company.

GLUCOPHAGE® is a registered trademark of Merck Santé S.A.S., an associate of Merck KGaA of Darmstadt, Germany. Licensed to Bristol-Myers Squibb Company.

Micronase® is a registered trademark of Pharmacia & Upjohn Company.

Distributed by:
Bristol-Myers Squibb Company
Princeton, NJ 08543 USA

1158884A6
Rev May 2010

Relabeling and Repackaging by:
Physicians Total Care, Inc.
Tulsa, Oklahoma 74146

PATIENT INFORMATION ABOUT
GLUCOVANCE® (Glyburide and Metformin HCl) Tablets

BOXED WARNING

WARNING: A small number of people who have taken metformin hydrochloride have developed a serious condition called lactic acidosis. Properly functioning kidneys are needed to help prevent lactic acidosis. Most people with kidney problems should not take GLUCOVANCE. (See Question Nos. 9-13.)

Q1. Why do I need to take GLUCOVANCE?

Your doctor has prescribed GLUCOVANCE to treat your type 2 diabetes. This is also known as non-insulin-dependent diabetes mellitus.

Q2. What is type 2 diabetes?

People with diabetes are not able to make enough insulin and/or respond normally to the insulin their body does make. When this happens, sugar (glucose) builds up in the blood. This can lead to serious medical problems, including kidney damage, amputations, and blindness. Diabetes is also closely linked to heart disease. The main goal of treating diabetes is to lower your blood sugar to a normal level.

Q3. Why is it important to control type 2 diabetes?

The main goal of treating diabetes is to lower your blood sugar to a normal level. Studies have shown that good control of blood sugar may prevent or delay complications, such as heart disease, kidney disease, or blindness.

Q4. How is type 2 diabetes usually controlled?

High blood sugar can be lowered by diet and exercise, a number of oral medications, and insulin injections. Before taking GLUCOVANCE you should first try to control your diabetes by exercise and weight loss. Even if you are taking GLUCOVANCE, you should still exercise and follow the diet recommended for your diabetes.

Q5. Does GLUCOVANCE work differently from other glucose-control medications?

Yes, it does. GLUCOVANCE combines 2 glucose-lowering drugs, glyburide and metformin. These 2 drugs work together to improve the different metabolic defects found in type 2 diabetes. Glyburide lowers blood sugar primarily by causing more of the body’s own insulin to be released, and metformin lowers blood sugar, in part, by helping your body use your own insulin more effectively. Together, they are efficient in helping you to achieve better glucose control.

Q6. What happens if my blood sugar is still too high?

When blood sugar cannot be lowered enough by GLUCOVANCE your doctor may prescribe injectable insulin or take other measures to control your diabetes.

Q7. Can GLUCOVANCE cause side effects?

GLUCOVANCE, like all blood sugar-lowering medications, can cause side effects in some patients. Most of these side effects are minor. However, there are also serious, but rare, side effects related to GLUCOVANCE (see Q9-Q13).

Q8. What are the most common side effects of GLUCOVANCE?

The most common side effects of GLUCOVANCE are normally minor ones such as diarrhea, nausea, and upset stomach. If these side effects occur, they usually occur during the first few weeks of therapy. Taking your GLUCOVANCE with meals can help reduce these side effects.

Less frequently, symptoms of hypoglycemia (low blood sugar), such as lightheadedness, dizziness, shakiness, or hunger may occur. The risk of hypoglycemic symptoms increases when meals are skipped, too much alcohol is consumed, or heavy exercise occurs without enough food. Following the advice of your doctor can help you to avoid these symptoms.

Q9. Are there any serious side effects that GLUCOVANCE can cause?

People who have a condition known as glucose-6-phosphate dehydrogenase (G6PD) deficiency and who take GLUCOVANCE may develop hemolytic anemia (fast breakdown of red blood cells). G6PD deficiency usually runs in families. Tell your doctor if you or any members of your family have been diagnosed with G6PD deficiency before you start taking GLUCOVANCE.

GLUCOVANCE rarely causes serious side effects. The most serious side effect that GLUCOVANCE can cause is called lactic acidosis.

Q10. What is lactic acidosis and can it happen to me?

Lactic acidosis is caused by a buildup of lactic acid in the blood. Lactic acidosis associated with metformin is rare and has occurred mostly in people whose kidneys were not working normally. Lactic acidosis has been reported in about 1 in 33,000 patients taking metformin over the course of a year. Although rare, if lactic acidosis does occur, it can be fatal in up to half the cases.

It’s also important for your liver to be working normally when you take GLUCOVANCE. Your liver helps remove lactic acid from your bloodstream.

Your doctor will monitor your diabetes and may perform blood tests on you from time to time to make sure your kidneys and your liver are functioning normally.

There is no evidence that GLUCOVANCE causes harm to the kidneys or liver.

Q11. Are there other risk factors for lactic acidosis?

Your risk of developing lactic acidosis from taking GLUCOVANCE is very low as long as your kidneys and liver are healthy. However, some factors can increase your risk because they can affect kidney and liver function. You should discuss your risk with your doctor.

You should not take GLUCOVANCE if:

- You have chronic kidney or liver problems
- You have congestive heart failure which is treated with medications, eg, digoxin (Lanoxin®) or furosemide (Lasix®)
- You drink alcohol excessively (all the time or short-term “binge” drinking)
- You are seriously dehydrated (have lost a large amount of body fluids)
- You are going to have certain x-ray procedures with injectable contrast agents
- You are going to have surgery
- You develop a serious condition, such as a heart attack, severe infection, or stroke
- You are ≥80 years of age and have NOT had your kidney function tested

Q12. What are the symptoms of lactic acidosis?

Some of the symptoms include: feeling very weak, tired or uncomfortable; unusual muscle pain; trouble breathing; unusual or unexpected stomach discomfort; feeling cold; feeling dizzy or lightheaded; or suddenly developing a slow or irregular heartbeat.

If you notice these symptoms, or if your medical condition has suddenly changed, stop taking GLUCOVANCE tablets and call your doctor right away. Lactic acidosis is a medical emergency that must be treated in a hospital.

Q13. What does my doctor need to know to decrease my risk of lactic acidosis?

Tell your doctor if you have an illness that results in severe vomiting, diarrhea, and/or fever, or if your intake of fluids is significantly reduced. These situations can lead to severe dehydration, and it may be necessary to stop taking GLUCOVANCE temporarily.

You should let your doctor know if you are going to have any surgery or specialized x-ray procedures that require injection of contrast agents. GLUCOVANCE therapy will need to be stopped temporarily in such instances.

Q14. Can I take GLUCOVANCE with other medications?

Remind your doctor that you are taking GLUCOVANCE when any new drug is prescribed or a change is made in how you take a drug already prescribed. GLUCOVANCE may interfere with the way some drugs work and some drugs may interfere with the action of GLUCOVANCE.

Q15. What if I become pregnant while taking GLUCOVANCE?

Tell your doctor if you plan to become pregnant or have become pregnant. As with other oral glucose-control medications, you should not take GLUCOVANCE during pregnancy.

Usually your doctor will prescribe insulin while you are pregnant. As with all medications, you and your doctor should discuss the use of GLUCOVANCE if you are nursing a child.

Q16. How do I take GLUCOVANCE?

Your doctor will tell you how many GLUCOVANCE tablets to take and how often. This should also be printed on the label of your prescription. You will probably be started on a low dose of GLUCOVANCE and your dosage will be increased gradually until your blood sugar is controlled.

Q17. Where can I get more information about GLUCOVANCE?

This leaflet is a summary of the most important information about GLUCOVANCE. If you have any questions or problems, you should talk to your doctor or other healthcare provider about type 2 diabetes as well as GLUCOVANCE and its side effects. There is also a leaflet (package insert) written for health professionals that your pharmacist can let you read.

GLUCOVANCE® is a registered trademark of Merck Santé S.A.S., an associate of Merck KGaA of Darmstadt, Germany. Licensed to Bristol-Myers Squibb Company.

Other brands listed are the trademarks of their respective owners.

Distributed by:
Bristol-Myers Squibb Company
Princeton, NJ 08543 USA

1158884A6
Rev May 2010

PACKAGE LABEL

-----------------------------------------
REPRESENTATIVE PACKAGING

See How Supplied section for a complete list of available packages of GLUCOVANCE.

100 Tablets
NDC 54868-4609-1

GLUCOVANCE®
(Glyburide and Metformin HCl) Tablets
2.5 mg/500 mg
Rx only